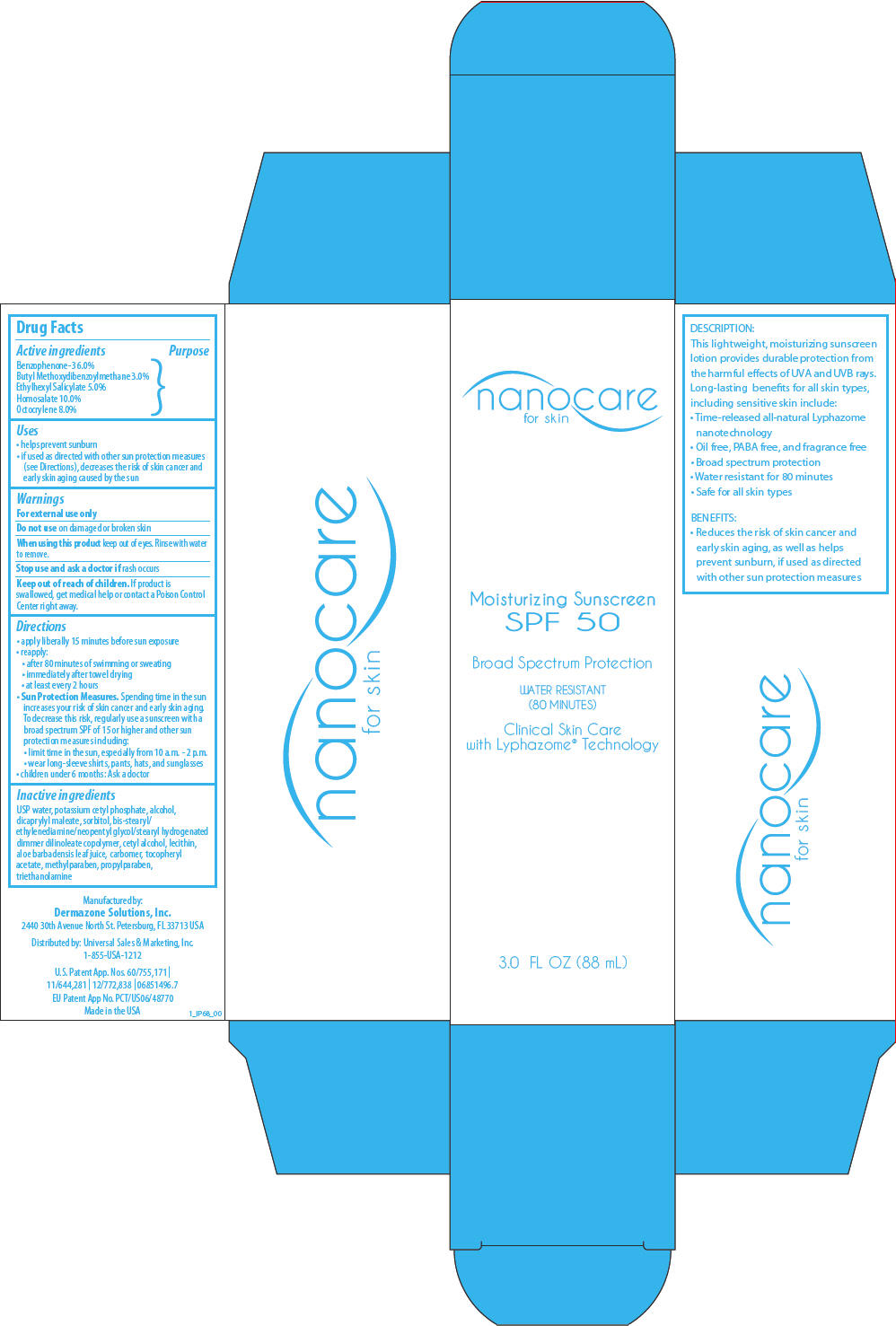 DRUG LABEL: nanocare 
NDC: 58466-033 | Form: LOTION
Manufacturer: Deramzone Solutions, Inc.
Category: otc | Type: HUMAN OTC DRUG LABEL
Date: 20121207

ACTIVE INGREDIENTS: Benzophenone 60 mg/1 mL; Avobenzone 30 mg/1 mL; Octisalate 50 mg/1 mL; Homosalate 100 mg/1 mL; Octocrylene 80 mg/1 mL
INACTIVE INGREDIENTS: water; potassium cetyl phosphate; alcohol; dioctyl maleate; sorbitol; cetyl alcohol; aloe vera leaf; .alpha.-tocopherol acetate; methylparaben; propylparaben; trolamine

nanocare for skin
Moisturizing Sunscreen SPF 50

Drug Facts

Active ingredients

Benzophenone-3 6.0%
Butyl Methoxydibenzoylmethane 3.0%
Ethylhexyl Salicylate 5.0%
Homosalate 10.0%
Octocrylene 8.0%

Uses

- helps prevent sunburn
- if used as directed with other sun protection measures (see Directions), decreases the risk of skin cancer and early skin aging caused by the sun

Warnings

For external use only

Do not use on damaged or broken skin

When using this product keep out of eyes. Rinse with water to remove.

Stop use and ask a doctor if rash occurs

Keep out of reach of children. If product is swallowed, get medical help or contact a Poison Control Center right away.

Directions

- apply liberally 15 minutes before sun exposure
- reapply:
  - after 80 minutes of swimming or sweating
  - immediately after towel drying
  - at least every 2 hours
- Sun Protection Measures. Spending time in the sun increases your risk of skin cancer and early skin aging. To decrease this risk, regularly use a sunscreen with a broad spectrum SPF of 15 or higher and other sun protection measures including:
  - limit time in the sun, especially from 10 a.m. - 2 p.m.
  - wear long-sleeve shirts, pants, hats, and sunglasses
- children under 6 months: Ask a doctor

Inactive ingredients

USP water, potassium cetyl phosphate, alcohol, dicaprylyl maleate, sorbitol, bis-stearyl/ethylenediamine/neopentyl glycol/stearyl hydrogenated dimmer dilinoleate copolymer, cetyl alcohol, lecithin, aloe barbadensis leaf juice, carbomer, tocopheryl acetate, methylparaben, propylparaben, triethanolamine

Manufactured by:
Dermazone Solutions, Inc.
2440 30th Avenue North St. Petersburg, FL 33713 USA

Distributed by: Universal Sales & Marketing, Inc.

PRINCIPAL DISPLAY PANEL - 88 mL Tube Carton

nanocare
for skin

Moisturizing Sunscreen
SPF 50

Broad Spectrum Protection

WATER RESISTANT
(80 MINUTES)

Clinical Skin Care
with Lyphazome® Technology

3.0 FL OZ (88 mL)